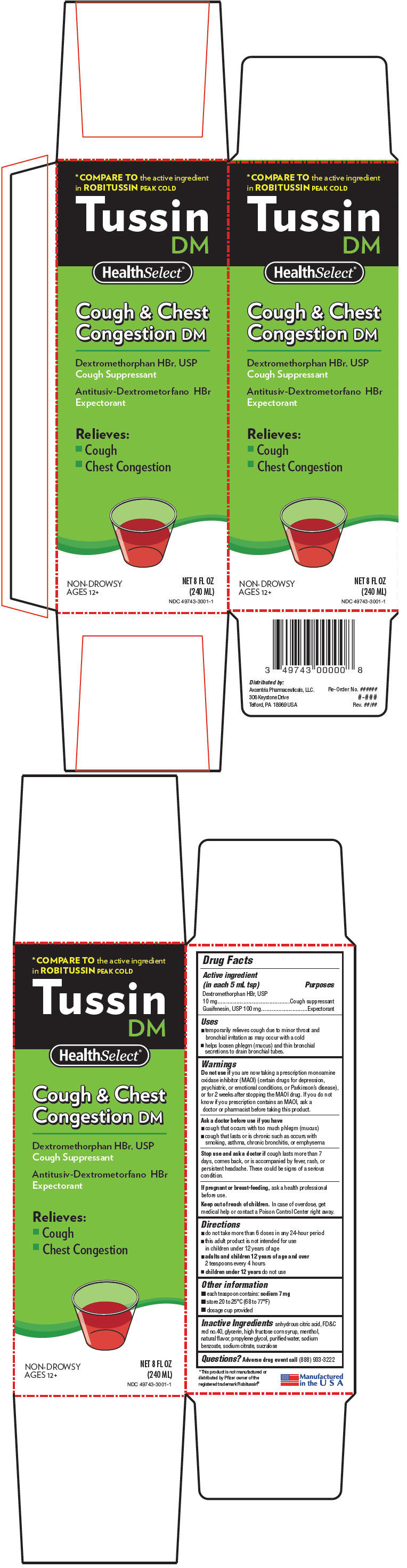 DRUG LABEL: SelectHealth Tussin DM
NDC: 49743-3001 | Form: LIQUID
Manufacturer: Axcentria Pharmaceuticals, LLC.
Category: otc | Type: HUMAN OTC DRUG LABEL
Date: 20110826

ACTIVE INGREDIENTS: Guaifenesin 100 mg/5 mL
INACTIVE INGREDIENTS: Menthol; Citric Acid Monohydrate; Sodium Benzoate; Saccharin Sodium; Glycerin

Tussin
DM

Drug Facts

ACTIVE INGREDIENT

Active ingredient (in each 5 mL tsp) | Purposes
Dextromethorphan HBr, USP 10 mg | Cough suppressant
Guaifenesin, USP 100 mg | Expectorant

Uses

- temporarily relieves cough due to minor throat and bronchial irritation as may occur with a cold
- helps loosen phlegm (mucus) and thin bronchial secretions to drain bronchial tubes.

Warnings

Do not use if you are now taking a prescription monoamine oxidase inhibitor (MAOI) (certain drugs for depression, psychiatric, or emotional conditions, or Parkinson's disease), or for 2 weeks after stopping the MAOI drug. If you do not know if you prescription contains an MAOI, ask a doctor or pharmacist before taking this product.

Ask a doctor before use if you have

- cough that occurs with too much phlegm (mucus)
- cough that lasts or is chronic such as occurs with smoking, asthma, chronic bronchitis, or emphysema

Stop use and ask a doctor if cough lasts more than 7 days, comes back, or is accompanied by fever, rash, or persistent headache. These could be signs of a serious condition.

PREGNANCY OR BREAST FEEDING

If pregnant or breast-feeding, ask a health professional before use.

Keep out of reach of children. In case of overdose, get medical help or contact a Poison Control Center right away.

Directions

- do not take more than 6 doses in any 24-hour period
- this adult product is not intended for use
  in children under 12 years of age
- adults and children 12 years of age and over
  2 teaspoons every 4 hours
- children under 12 years do not use

Other information

- each teaspoon contains: sodium 7 mg
- store 20 to 25°C (68 to 77°F)
- dosage cup provided

Inactive Ingredients

anhydrous citric acid, FD&C red no.40, glycerin, high fructose corn syrup, menthol, natural flavor, propylene glycol, purified water, sodium benzoate, sodium citrate, sucralose

Questions?

Adverse drug event call (888) 933-3222

Distributed by:
Axcentria Pharmaceuticals, LLC.
306 Keystone Drive
Telford, PA 18969 USA

PRINCIPAL DISPLAY PANEL - 240 ML Bottle Carton

*COMPARE TO the active ingredient
in ROBITUSSIN PEAK COLD

Tussin
DM

HealthSelect®

Cough & Chest
Congestion DM

Dextromethorphan HBr, USP
Cough Suppressant

Antitusiv-Dextrometorfano HBr
Expectorant

Relieves:

- Cough
- Chest Congestion

NON-DROWSY
AGES 12+

NET 8 FL OZ
(240 ML)
NDC 49743-3001-1